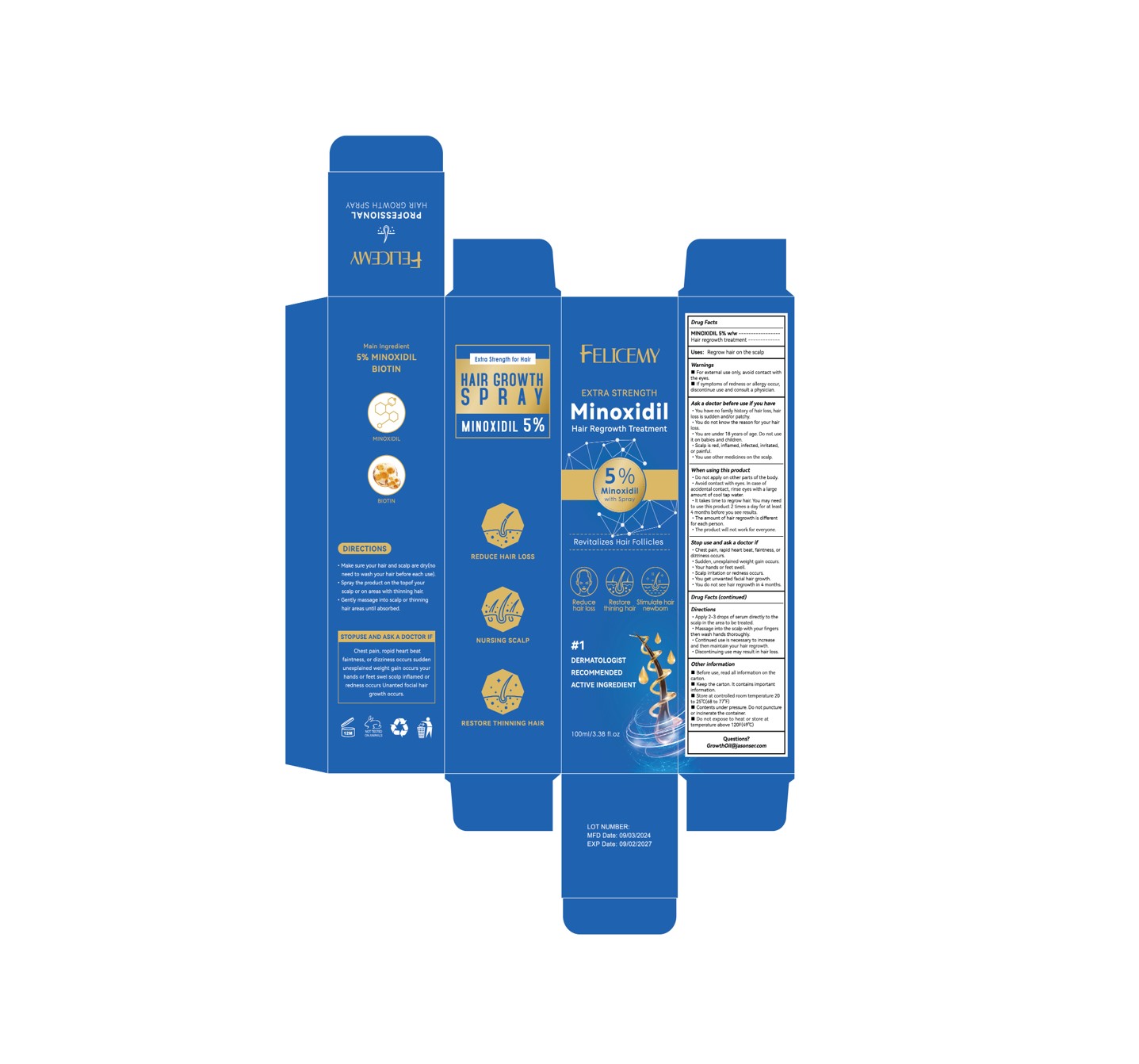 DRUG LABEL: Minoxidil hair growth serum
NDC: 84867-005 | Form: LIQUID
Manufacturer: Jiashen International Trade Limited
Category: otc | Type: HUMAN OTC DRUG LABEL
Date: 20251109

ACTIVE INGREDIENTS: MINOXIDIL 50 mg/100 mL
INACTIVE INGREDIENTS: 1,2-HEXANEDIOL; MYRISTOYL PENTAPEPTIDE-4; PROPYLENE GLYCOL; GLYCERYL CAPRYLATE; SODIUM HYALURONATE; ALCOHOL; CAPRYLHYDROXAMIC ACID; SOPHORA FLAVESCENS ROOT; AQUA; CAFFEINE; ACETYL TETRAPEPTIDE-3

ACTIVE INGREDIENT

MINOXIDIL 5%

INACTIVE INGREDIENT

CAFFEINE
ACETYL TETRAPEPTIDE-3
MYRISTOYL PENTAPEPTIDE-4
1,2-HEXANEDIOL
SOPHORA FLAVESCENS ROOT EXTRACT
SODIUM HYALURONATE
AQUA
PROPYLENE GLYCOL
ALCOHOL
GLYCERYL CAPRYLATE
CAPRYLHYDROXAMIC ACID

PURPOSE

REDUCE HAIR LOSS
NURSING SCALP
RESTORE THINNING HAIR

WARNINGS

For external use only, avoid contact withthe eyes.lf symptoms of redness or allergy occur,discontinue use and consult a physician.

STOP USE

Chest pain, ropid heart beatfaintness, or dizziness occurs suddenunexplained weight gain occurs yourhands or feet swel scolp inflamed orredness occurs Unanted focial hair
growth occurs.

KEEP OUT OF REACH OF CHILDREN

You are under 18 years of age. Do not useit on babies and children，keep out of reach of childrean

INDICATIONS AND USAGE

Make sure your hair and scalp are dry(noneed to wash your hair before each use).Spray the product on the topof yourscalp or on areas with thinning hair.* Gently massage into scalp or thinninghair areas until absorbed.

DOSAGE AND ADMINISTRATION

Apply 2-3 drops of serum directly to thescalp in the area to be treated.Massage into the scalp with your fingersthen wash hands thoroughly..Continued use is necessary to increaseand then maintain your hair regrowth.*Discontinuing use may result in hair loss.

When using this product
* Do not apply on other parts of the body*Avoid contact with eyes. in case ofaccidental contact, rinse eyes with a largeamount of cool tap water..lt takes time to regrow hair. You may needto use this product 2 times a day for at least4 months before you see results.*The amount of hair regrowth is differentfor each person.* The product will not work for everyone.